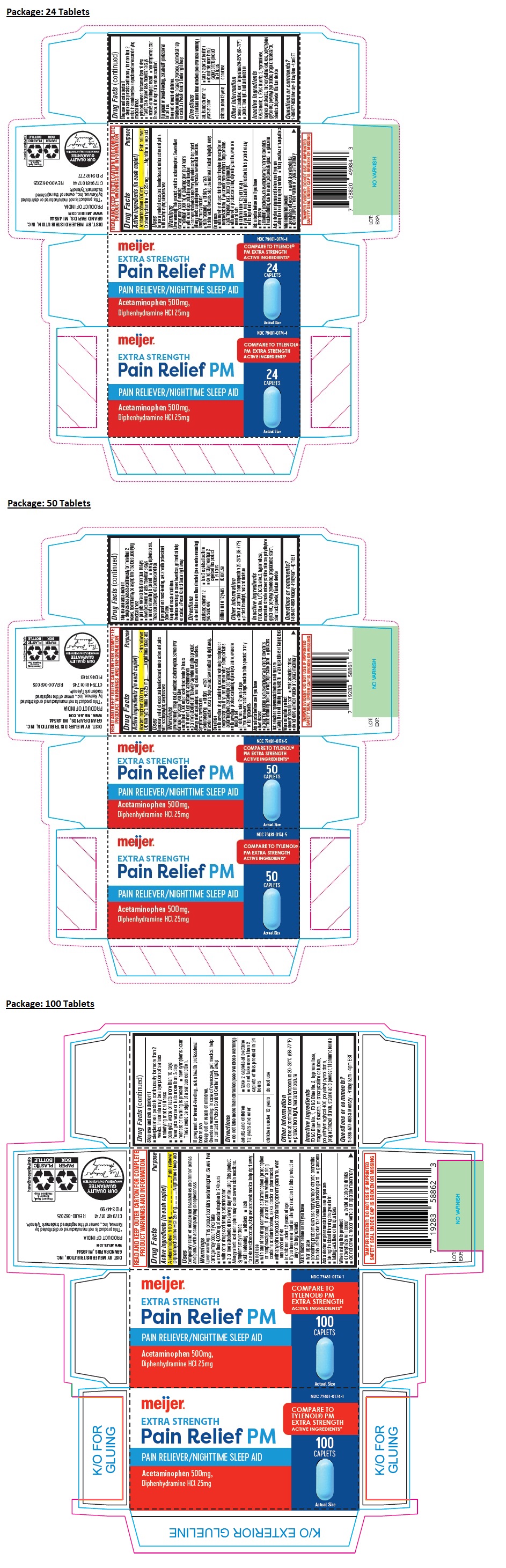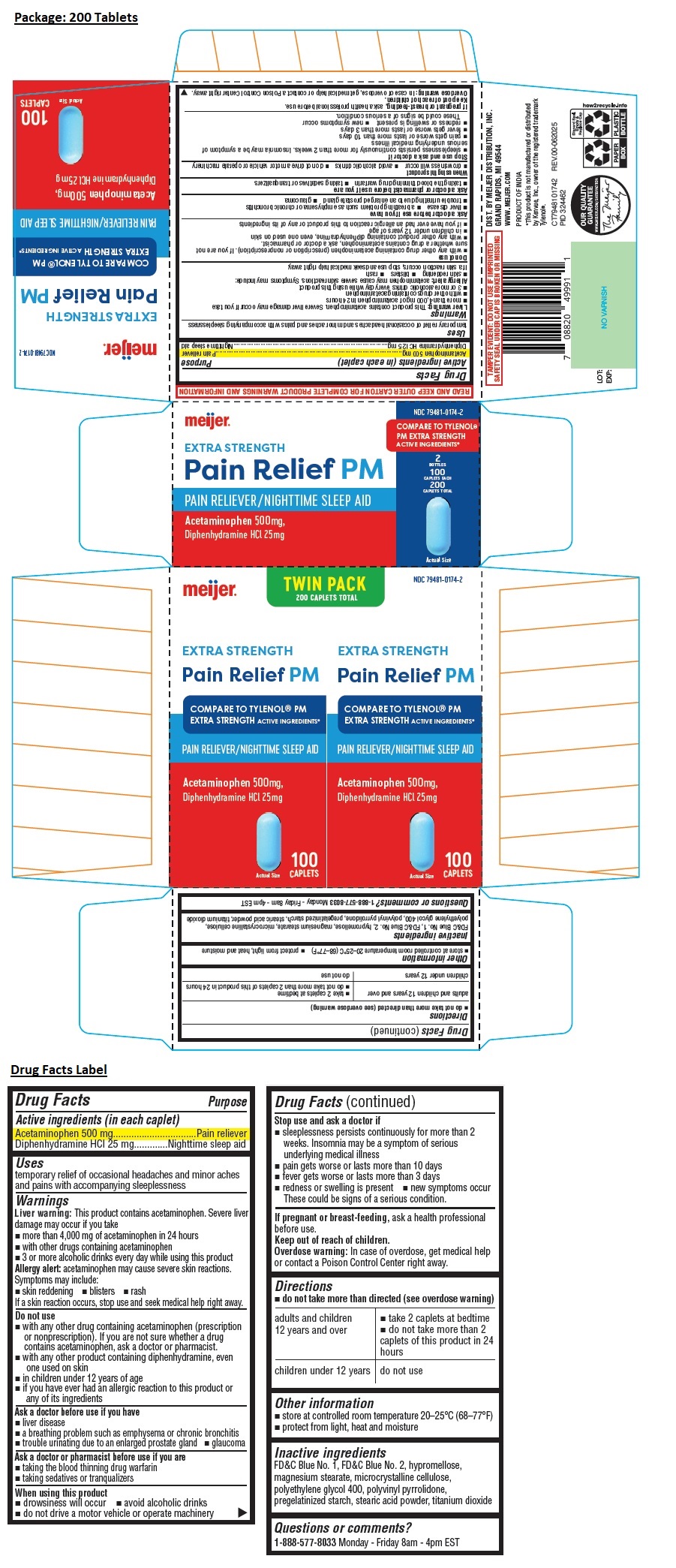 DRUG LABEL: meijer EXTRA STRENGTH Pain Relief PM CAPLET
NDC: 79481-0174 | Form: TABLET
Manufacturer: Meijer, Inc.
Category: otc | Type: HUMAN OTC DRUG LABEL
Date: 20250805

ACTIVE INGREDIENTS: ACETAMINOPHEN 500 mg/1 1; DIPHENHYDRAMINE HYDROCHLORIDE 25 mg/1 1
INACTIVE INGREDIENTS: FD&C BLUE NO. 1; FD&C BLUE NO. 2; HYPROMELLOSE, UNSPECIFIED; MAGNESIUM STEARATE; MICROCRYSTALLINE CELLULOSE; POLYETHYLENE GLYCOL 400; POVIDONE K30; STARCH, CORN; STEARIC ACID; TITANIUM DIOXIDE

meijer® EXTRA STRENGTH Pain Relief PM CAPLET

Active ingredients (in each caplet)

Acetaminophen 500 mg
Diphenhydramine HCl 25 mg

Purpose

Pain reliever
Nighttime sleep aid

Uses

temporary relief of occasional headaches and minor aches and pains with accompanying sleeplessness

Warnings

Liver warning: This product contains acetaminophen. Severe liver damage may occur if you take
• more than 4,000 mg of acetaminophen in 24 hours
• with other drugs containing acetaminophen
• 3 or more alcoholic drinks every day while using this product
Allergy alert: acetaminophen may cause severe skin reactions.
Symptoms may include:
• skin reddening • blisters • rash
If a skin reaction occurs, stop use and seek medical help right away.

Do not use
• with any other drug containing acetaminophen (prescription or nonprescription). If you are not sure whether a drug contains acetaminophen, ask a doctor or pharmacist.
• with any other product containing diphenhydramine, even one used on skin
• in children under 12 years of age
• if you have ever had an allergic reaction to this product or any of its ingredients

Ask a doctor before use if you have
• liver disease
• a breathing problem such as emphysema or chronic bronchitis
• trouble urinating due to an enlarged prostate gland • glaucoma

Ask a doctor or pharmacist before use if you are
• taking the blood thinning drug warfarin
• taking sedatives or tranquilizers

When using this product
• drowsiness will occur • avoid alcoholic drinks
• do not drive a motor vehicle or operate machinery

Stop use and ask a doctor if
• sleeplessness persists continuously for more than 2 weeks. Insomnia may be a symptom of serious underlying medical illness
• pain gets worse or lasts more than 10 days
• fever gets worse or lasts more than 3 days
• redness or swelling is present • new symptoms occur
These could be signs of a serious condition.

If pregnant or breast-feeding, ask a health professional before use.

Keep out of reach of children.
Overdose warning: In case of overdose, get medical help or contact a Poison Control Center right away.

Directions

• do not take more than directed (see overdose warning)

adults and children 12 years and over | • take 2 caplets at bedtime • do not take more than 2 caplets of this product in 24 hours
children under 12 years | do not use

Other information

• store at controlled room temperature 20–25°C (68–77°F)
• protect from light, heat and moisture

Inactive ingredients

FD&C Blue No. 1, FD&C Blue No. 2, hypromellose, magnesium stearate, microcrystalline cellulose, polyethylene glycol 400, polyvinyl pyrrolidone,
pregelatinized starch, stearic acid powder, titanium dioxide

Questions or comments?

1-888-577-8033 Monday - Friday 8am - 4pm EST

COMPARE TO TYLENOL® PM EXTRA STRENGTH ACTIVE INGREDIENTS*

READ AND KEEP OUTER CARTON FOR COMPLETE PRODUCT WARNINGS AND INFORMATION

DIST. BY MEIJER DISTRIBUTION, INC.
GRAND RAPIDS, MI 49544

WWW.MEIJER.COM

PRODUCT OF INDIA

*This product is not manufactured or distributed by Kenvue, Inc., owner of the registered trademark Tylenol®

TAMPER EVIDENT: DO NOT USE IF IMPRINTED SAFETY SEAL UNDER CAP IS BROKEN OR MISSING